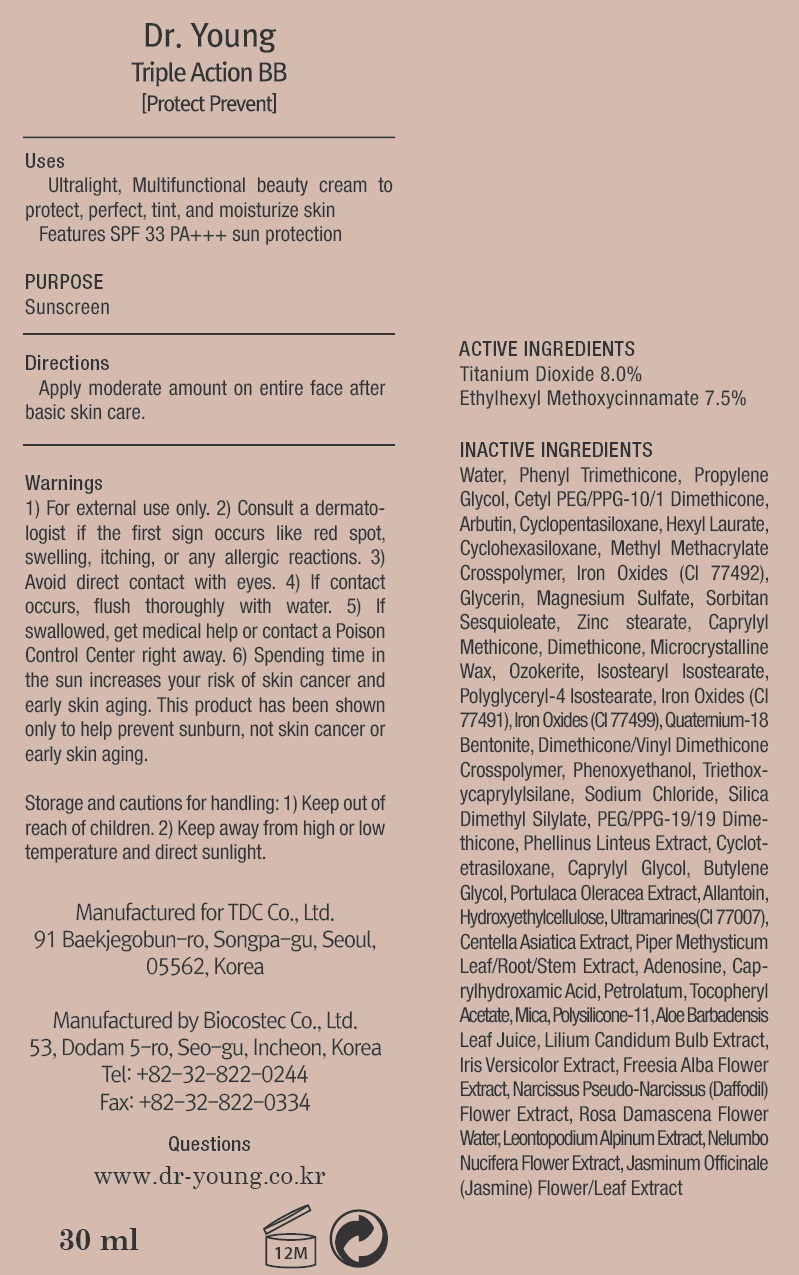 DRUG LABEL: Dr Young Protect Prevent Triple Action BB
NDC: 43948-1330 | Form: CREAM
Manufacturer: Tdc, Co. Ltd
Category: otc | Type: HUMAN OTC DRUG LABEL
Date: 20171114

ACTIVE INGREDIENTS: Titanium Dioxide 2.40 g/30 mL; Octinoxate 2.25 g/30 mL
INACTIVE INGREDIENTS: Water; Phenyl Trimethicone

ACTIVE INGREDIENT

Active ingredients: Titanium Dioxide 8.0%, Ethylhexyl Methoxycinnamate 7.5%

INACTIVE INGREDIENT

Inactive ingredients: Water, Phenyl Trimethicone, Propylene Glycol, Cetyl PEG/PPG-10/1 Dimethicone, Arbutin, Cyclopentasiloxane, Hexyl Laurate, Cyclohexasiloxane, Methyl Methacrylate Crosspolymer, Iron Oxides (CI 77492), Glycerin, Magnesium Sulfate, Sorbitan Sesquioleate, Zinc stearate, Caprylyl Methicone, Dimethicone, Microcrystalline Wax, Ozokerite, Isostearyl Isostearate, Polyglyceryl-4 Isostearate, Iron Oxides (CI 77491), Iron Oxides (CI 77499), Quaternium-18 Bentonite, Dimethicone/Vinyl Dimethicone Crosspolymer, Phenoxyethanol, Triethoxycaprylylsilane, Sodium Chloride, Silica Dimethyl Silylate, PEG/PPG-19/19 Dimethicone, Phellinus Linteus Extract, Cyclotetrasiloxane, Caprylyl Glycol, Butylene Glycol, Portulaca Oleracea Extract, Allantoin, Hydroxyethylcellulose, Ultramarines(CI 77007), Centella Asiatica Extract, Piper Methysticum Leaf/Root/Stem Extract, Adenosine, Caprylhydroxamic Acid, Petrolatum, Tocopheryl Acetate, Mica, Polysilicone-11, Aloe Barbadensis Leaf Juice, Lilium Candidum Bulb Extract, Iris Versicolor Extract, Freesia Alba Flower Extract, Narcissus Pseudo-Narcissus (Daffodil) Flower Extract, Rosa Damascena Flower Water, Leontopodium Alpinum Extract, Nelumbo Nucifera Flower Extract, Jasminum Officinale (Jasmine) Flower/Leaf Extract

PURPOSE

Purpose: Sunscreen

WARNINGS

Warning: 1) For external use only. 2) Consult a dermatologist if the first sign occurs like red spot, swelling, itching, or any allergic reactions. 3) Avoid direct contact with eyes. 4) If contact occurs, flush thoroughly with water. 5) If swallowed, get medical help or contact a Poison Control Center right away. 6) Spending time in the sun increases your risk of skin cancer and early skin aging. This product has been shown only to help prevent sunburn, not skin cancer or early skin aging.

Storage and cautions for handling: 1) Keep out of reach of children. 2) Keep away from high or low temperature and direct sunlight.

DESCRIPTION

Uses: - Ultralight, Multifunctional beauty cream to protect, perfect, tint, and moisturize skin - Features SPF 33 PA+++ sun protection

Directions: Apply moderate amount on entire face after basic skin care.